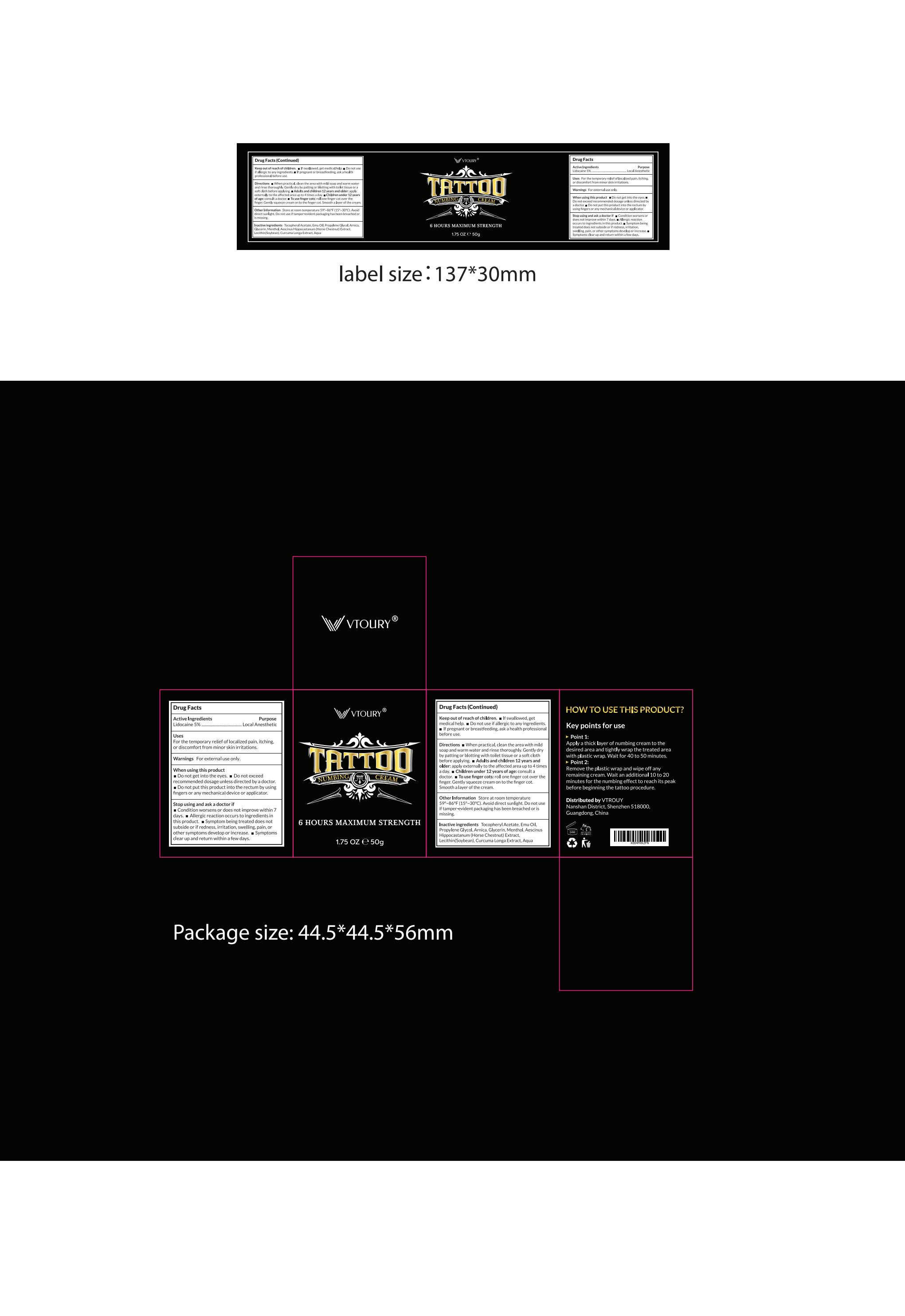 DRUG LABEL: VTROUY Tattoo Numbing Cream
NDC: 85150-004 | Form: CREAM
Manufacturer: Guangzhou Zanming Trading Co., Ltd.
Category: otc | Type: HUMAN OTC DRUG LABEL
Date: 20250219

ACTIVE INGREDIENTS: LIDOCAINE 5 g/100 g
INACTIVE INGREDIENTS: PROPYLENE GLYCOL; HORSE CHESTNUT; SOYBEAN; EMU OIL; MENTHOL; ARNICA MONTANA FLOWER; CURCUMA LONGA (TURMERIC) ROOT POWDER; AQUA; ALPHA-TOCOPHEROL ACETATE; GLYCERIN

85150-004

Active Ingredient

Lidocaine 5%

Purpose

Local Anesthetic

Use

For the temporary relief of localized pain, itching, or discomfort from minor skin irritations.

Warnings

For external use only.

Do not use

If allergic to any ingredients.

When Using

Do not get into the eyes. Do not exceed recommended dosage unless directed by a doctor. Do not put this product into the rectum by using fingers or any mechanical device or applicator.

Stop Use

If condition worsens or does not improve within 7 days. If allergic reaction occurs to ingredients in this product. If symptom being treated does not subside or if redness, irritation, swelling, pain, or other symptoms develop or increase. If symptoms clear up and return within a few days.

Ask Doctor

If pregnant or breastfeeding. If condition worsens or does not improve within 7 days. If allergic reaction occurs to ingredients in this product. If symptom being treated does not subside or if redness, irritation, swelling, pain, or other symptoms develop or increase. If symptoms clear up and return within a few days.

Keep Oot Of Reach Of Children

Keep out of reach of children. If swallowed, get medical help.

Directions

When practical, clean the area with mild soap and warm water and rinse thoroughly. Gently dry by patting or blotting with toilet tissue or a soft cloth before applying. Adults and children 12 years and older: apply externally to the affected area up to 4 times a day. Children under 12 years: consult a doctor. To use finger cots: roll one finger cot over the finger. Gently squeeze cream on to the finger cot. Smooth a layer of the cream.

Other information

Store at room temperature 59° - 86°F (15° - 30°C). Avoid direct sunlight. Do not use if tamper - evident packaging has been breached or is missing.

Inactive ingredients

Tocopheryl Acetate, Emu Oil, Propylene Glycol, Arnica, Glycerin, Menthol, Aescinns Hippocastanum (Horse Chestnut) Extract, Lecithin(Soybean), Curcuma Longa Extract, Aqua